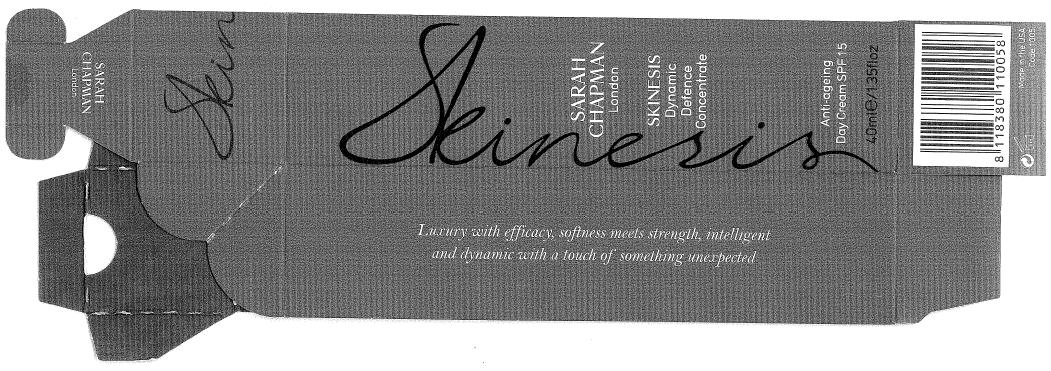 DRUG LABEL: Dynamic Defence Concentrate Anti-Ageing Day  SPF 15
NDC: 49678-1005 | Form: CREAM
Manufacturer: SARAH CHAPMAN LTD
Category: otc | Type: HUMAN OTC DRUG LABEL
Date: 20100709

ACTIVE INGREDIENTS: OCTINOXATE 50 mg/1 mL; OCTISALATE 50 mg/1 mL; OXYBENZONE 30 mg/1 mL; AVOBENZONE 20 mg/1 mL

Drug Facts

ACTIVE INGREDIENTS:

1. OCTINOXATE (OCTYL METHOXYCINNAMATE) 5%

2. OCTISALATE (OCTYL SALICYLATE) 5%

3. OXYBENZONE (BENZOPHENONE-3) 3%

4. AVOBENZONE (1-4-TERT-BUTYLPHENYL-3-(4-METHOXYPHENYL) PROPANE-1,3-DIONE) 2%

INACTIVE INGREDIENTS:

PURIFIED WATER, C12 -15 ALKYL BENZOATE, DIMETHICONE, CAPRYLIC / CAPRIC TRIGLYCERIDE, GLYCERINE, RUMEX OCCIDENTALIS EXTRACT, C14-22 ALCOHOLS, CETYL ALCOHOL, CRAMBE ABYSSINICA SEED OIL, GLYCERYL STEARATE, PEG-100 STEARATE, TETRAHEXYLDECYL ASCORBATE, ARCTOSTAPHYLOW UVA URSI LEAF EXTRACT, TEPRENONE, PALMITOYL TETRAPEPTIDE 7, HYDROXYETHYL ACRYLATE / SODIUM ACRYOYDIMETHYL TAURATE COPOLYMER, BUTELENE GLYCOL, SQUALANE, C 12 - 20 ALKYL GLUCOSIDES, POLYSORBATE 60, SODIUM PCA, LECITHIN, PLANKTON EXTRACT, MANGIFERA INDICA SEED BUTTER, BUTYROSPERMUM PARKII, NYLON 12, YEAST POLYSACCHARADIES, PHYLLANTHUS EMBLICA FRUIT EXTRACT, RETINYL PALMITATE, UBIQUINONE, TOCOPHEROL ACETATE, PHENOXYEHTHANOL, CAPRYLYL GLYCOL, ETHYLHEXYLGLYCERINE, HEXYLENE GLYCOL, CERUS DEODORA WOOD OIL, IRIS FLORENTINA ROOT EXTRACT, ROSA CANINA FLOWER EXTRACT, JASMINUM OFFICINALE FLOWER EXTRACT, DISODIUM EDTA, HYDROXYDECYL UBIQUINONE, HYACINTHUS ORIENTALIS FLOWER EXTRACT, JASMINUM GRANDIFLORUM FLOWER WAX, SANTALUM ALBUM OIL, DIETHYLHEXYL SYRINGYLDENE MALONATE, PELARGONIUM GRAVEOLENS FLOWER OIL, ROSA DAMASCENA FLOWER OIL.

Other information on the back panel:
Fragranced with a subtle hint of jasmine, hyacinth and rose essential oils
Uses:
This advanced formula day cream for skins already used to high-potency skincare. Essential advice to all clients is to support the skin's natural defense with supercharged levels of vitamins A, C, antioxidants, omega-rich oils and broad spectrum SPF 15.
Dynamic Defence Concentrate contains all of these, many in potent double-strength. Revolutionary Renovage TM and Matrixyl TM 3000 peptide combine with triple skin-brighteners and precious iris, rose and jasmine. This helps to give an improved feeling of plumpness, appearance of clarity and restored natural moisture balance.
Tips for use: Smooth all over face, neck and chest every morning after Age-Repair Concentrate.

PACKAGE LABEL

Distributor:

Sarah Chapman Ltd, London SW3 3AE, UK

www.sarahchapman.net

Image of Carton:

SKINESIS

Dynamic Defence Concentrate

Anti-ageing Day Cream SPF 15

40ml/1.35floz